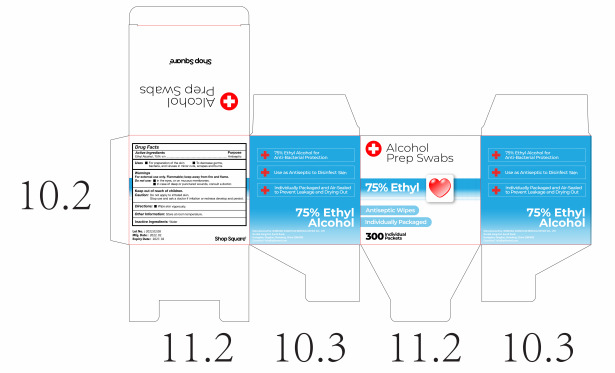 DRUG LABEL: ALCOHOL WIPES
NDC: 84231-001 | Form: CLOTH
Manufacturer: QINGDAO KANGYUAN MEDICAL DEVICE CO.,LTD
Category: otc | Type: HUMAN OTC DRUG LABEL
Date: 20240408

ACTIVE INGREDIENTS: ALCOHOL 75 g/100 g
INACTIVE INGREDIENTS: WATER

84231-001

Active Ingredient(s)

Ethyl Alcohol, 75% V/v

Purpose

Antiseptic

Use

■For preparation of the skin

■To decrease germs, bacteria, and viruses in minor cuts, scrapes and burns.

Warnings

For external use only. Flammable; keep away from fire and flame.

Do not use

- in the eyes, or on mucous membranes.
- In case of deep or punctured wounds, consult a doctor.

WHEN USING SECTION

When using this product keep out of eyes, ears, and mouth. In case of contact with eyes, rinse eyes thoroughly with water.
Stop use and ask a doctor if irritation or rash occurs. These may be signs of a serious condition.
Keep out of reach of children. If swallowed, get medical help or contact a Poison Control Center right away.

Stop use and ask a doctor if irritation or rash occurs. These may be signs of a serious condition.

Keep out of reach of children

Caution: Do not apply to iritated skin.

Stop use and ask a doctor if iritation or redness develop and persist.

Directions

Wipe skin vigorously.

Other information

Store at room temperature.

Inactive ingredients

Water